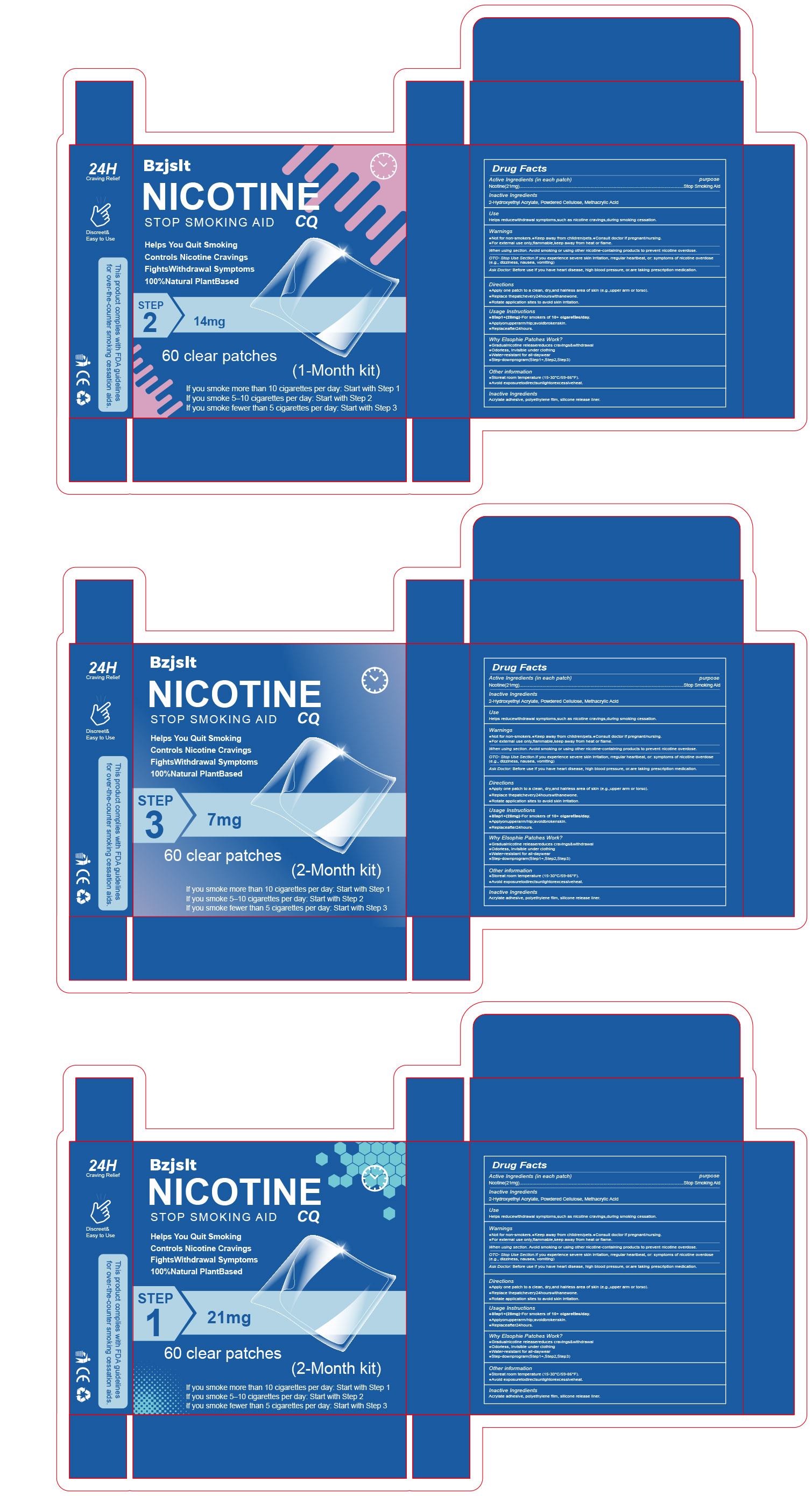 DRUG LABEL: Nicotine Stop Smoking AID
NDC: 87278-002 | Form: PATCH
Manufacturer: Guangxi Keyun E-commerce Co., Ltd.
Category: otc | Type: HUMAN OTC DRUG LABEL
Date: 20251211

ACTIVE INGREDIENTS: NICOTINE 21 mg/1 1
INACTIVE INGREDIENTS: 2-HYDROXYETHYL ACRYLATE; POLYETHYLENE; POWDERED CELLULOSE; ISOOCTYL ACRYLATE; SILICON DIOXIDE; METHACRYLIC ACID

87278-002 Nicotine Stop Smoking AID

ACTIVE INGREDIENT

Nicotine

PURPOSE

Stop Smoking Aid

INDICATIONS AND USAGE

Helps reducewithdrawal symptoms,such as nicotine cravings,during smoking cessation

WARNINGS

Not for non-smokers.
Keep away from children/pets.
Consult doctor if pregnant/nursing
For external use only,flammable,keep away from heat or flame.

Not for non-smokers.

WHEN USING

When using section. Avoid smoking or using other nicotine-containing products to prevent nicotine overdose

STOP USE

OTC- Stop Use Section.If you experience severe skin irritation, rregular heartbeat, or: symptoms of nicotine overdose
(e.g., dizziness, nausea, vomiting)

Keep away from children/pets.

DOSAGE AND ADMINISTRATION

Apply one patch to a clean, dry,and hairless area of skin (e.g.,upper arm or torso).
Replace thepatchevery24hourswithanewone.
Rotate application sites to avoid skin irritation.

INACTIVE INGREDIENT

2-Hydroxyethyl Acrylate
Powdered Cellulose
Methacrylic Acid
Acrylate Adhesive
Polyethylene Film
Silicone Release Liner